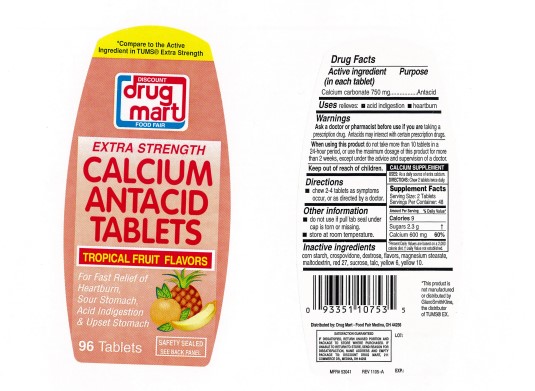 DRUG LABEL: Extra Strength Antacid Tropical Fruit
NDC: 53943-127 | Form: TABLET, CHEWABLE
Manufacturer: Discount Drug Mart, Inc
Category: otc | Type: Human OTC Drug Label
Date: 20250225

ACTIVE INGREDIENTS: CALCIUM CARBONATE 750 mg/1 1
INACTIVE INGREDIENTS: STARCH, CORN; DEXTROSE, UNSPECIFIED FORM; MAGNESIUM STEARATE; MALTODEXTRIN; SUCROSE; TALC; CROSPOVIDONE; D&C RED NO. 27 ALUMINUM LAKE; D&C YELLOW NO. 10 ALUMINUM LAKE; FD&C YELLOW NO. 6 ALUMINUM LAKE

Extra Strength Calcium Antacid Tropical Fruit Tablets

ACTIVE INGREDIENT (in each tablet)

Calcium carbonate 750 mg

PURPOSE

Antacid

USE(S)

relieves:

- acid indigestion
- heartburn

WARNINGS

.

ASK A DOCTOR OR PHARMACIST BEFORE USE IF YOU ARE

taking a prescription drug. Antacids may interact with certain prescription drugs.

WHEN USING THIS PRODUCT

do not take more than 10 tablets in a 24-hour period, or use the maximum dosage of this product for more than 2 weeks, except under the advice and supervision of a doctor.

KEEP OUT OF REACH OF CHILDREN

.

DIRECTIONS

- chew 2-4 tablets as symptoms occur, or as directed by a doctor.

OTHER INFORMATION

- do not use if printed seal under cap is torn or missing.
- store at room temperature.

INACTIVE INGREDIENTS

corn starch, crospovidone, D&C red 27 lake, D&C yellow 10 lake, dextrose, FD&C yellow 6 lake, flavors, magnesium stearate, maltodextrin, sucrose, talc.

PRINCIPAL DISPLAY PANEL

Discount drug mart

FOOD FAIR

EXTRA STRENGTH CALCIUM ANTACID TABLETS

TROPICAL FRUIT FLAVORS

For Fast Relief of

Heartburn,

Sour Stomach,

Acid Indigestion & Upset Stomach

96 Tablets

SAFETY SEALED
SEE BACK PANEL